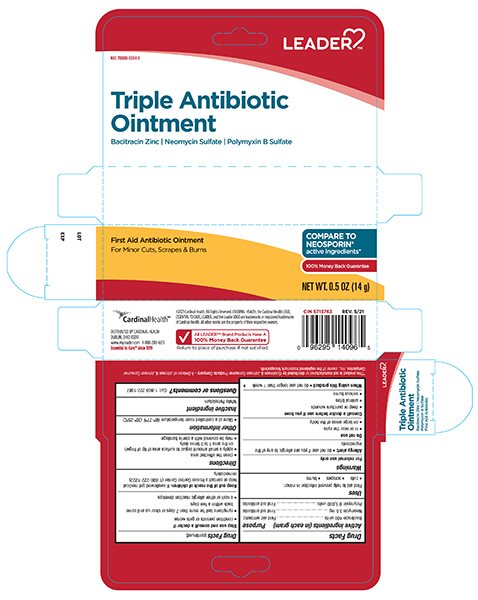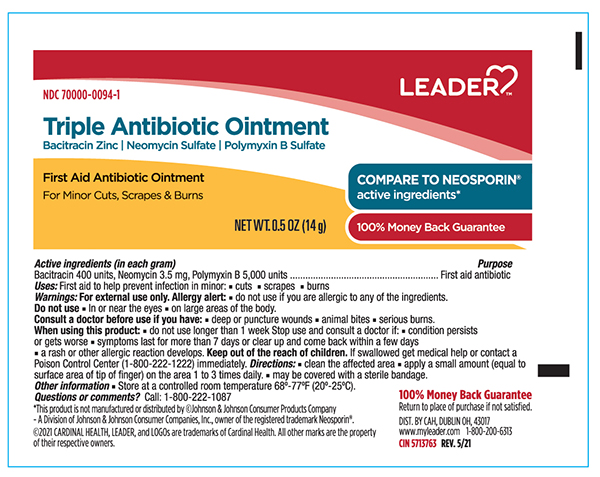 DRUG LABEL: Leader Triple Antibiotic
NDC: 70000-0094 | Form: OINTMENT
Manufacturer: Cardinal Health 110,Inc.
Category: otc | Type: HUMAN OTC DRUG LABEL
Date: 20240118

ACTIVE INGREDIENTS: Bacitracin Zinc 400 [USP'U]/1 g; NEOMYCIN SULFATE 3.5 mg/1 g; POLYMYXIN B SULFATE 5000 [USP'U]/1 g
INACTIVE INGREDIENTS: Petrolatum

Triple Antibiotic Ointment

Drug Facts

Active ingredients (In each gram)

Bacitracin 400 Units

Neomycin Sulfate 3.5 mg

Polymyxin B Sulfate 5,000 units

Purpose

First aid antibiotic

Uses

First aid to help prevent infection in minor:

- cuts
- scrapes
- burns

Warnings

For external use only

Allergy alert:

- do not use if you are allergic to any of the ingredients

Do not use

- in or near the eyes
- on large areas of the body

Consult a doctor before use if you have

- deep or puncture wounds
- animal bites
- serious burns

When using this product

- do not use longer than 1 week

Stop use and consult a doctor if

- condition persists or gets worse
- symptoms last for more than 7 days or clear up and come back within a few days
- a rash or other allergic reaction develops

KEEP OUT OF REACH OF CHILDREN

Keep out of the reach of children. If swallowed get medical help or contact a Poison Control Center immediately.

Directions

- clean the affected area
- apply a small amount (equal to surface area of tip of finger) on the area 1 to 3 times daily.
- may be covered with a sterile bandage

Other information

- Store at a controlled room temperature 20º-25ºC (68° to 77°F)

Inactive ingredient

Petrolatum

Principal Display Panel – Carton Label

Leader NDC 70000-0094-1

Triple Antibiotic Ointment USP

- Bacitracin Zinc
- Neomycin Sulfate
- Polymyxin B Sulfate

First Aid Antibiotic Ointment

NET WT. 0.5oz (14g)

Principal Display Panel – Tube Label

Leader NDC 70000-0094-1

Triple Antibiotic Ointment

- Bacitracin Zinc
- Neomycin Sulfate
- Polymyxin B Sulfate

First Aid Antibiotic Ointment

Protection against Infection

NET WT. 0.5oz (14g)